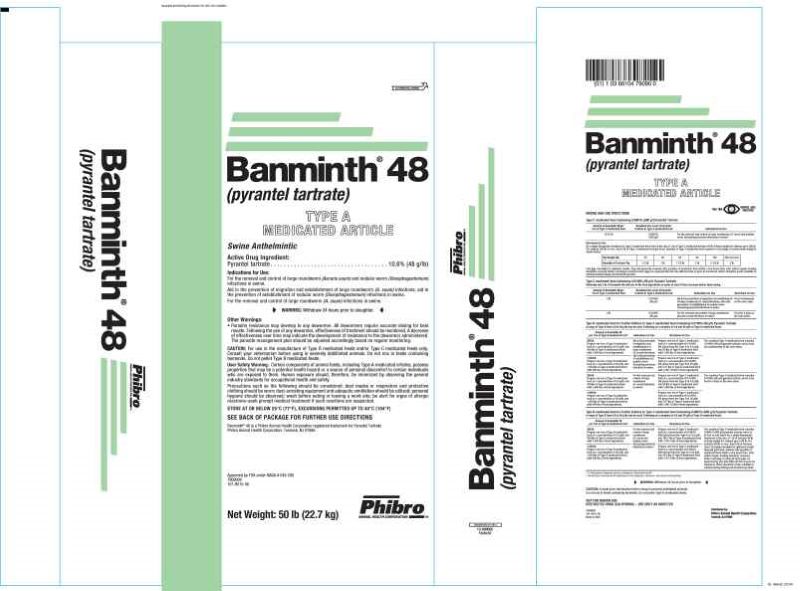 DRUG LABEL: Banminth 48
NDC: 66104-2391 | Form: POWDER
Manufacturer: Phibro Animal Health
Category: animal | Type: OTC TYPE A MEDICATED ARTICLE ANIMAL DRUG LABEL
Date: 20250310

ACTIVE INGREDIENTS: PYRANTEL 48 g/0.45 kg
INACTIVE INGREDIENTS: MINERAL OIL; CALCIUM CARBONATE; SOYBEAN

Banminth®48
(pyrantel tartrate)
TYPE A
MEDICATED ARTICLE

DESCRIPTION

Swine Anthelmintic

Active Drug Ingredient:

Pyrantel tartrate . . . . . . . . . . . . . . . . . . . . . . . . . . . . . . . . . . . 10.6% (48 g/lb)

Indications for Use:

For the removal and control of large roundworm (Ascaris suum) and nodular worm (Oesophagostomum)infections in swine.

Aid in the prevention of migration and establishment of large roundworm (A. suum) infections; aid in the prevention of establishment of nodular worm (Oesophagostomum)infections in swine.

For the removal and control of large roundworm (A. suum)infections in swine.

WARNING:

Withdraw 24 hours prior to slaughter.

Other Warning: Parasite resistance may develop to any dewormer. All dewormers require accurate dosing for best results. Following the use of any dewormer, effectiveness of treatment should be monitored. A decrease of effectiveness over time may indicate the development of resistance to the dewormer administered. The parasite management plan should be adjusted accordingly based on regular monitoring. CAUTION:

For use in the manufacture of complete swine feeds and/or swine protein supplement feeds only.

CAUTION:

Certain components of animal feeds, including medicated premixes, possess properties that may be a potential health hazard or a source of personal discomfort to certain individuals who are exposed to them. Human exposure should, therefore, be minimized by observing the general industry standards for occupational health and safety.

Precautions such as the following should be considered: dust masks or respirators and protective clothing should be worn; dust-arresting equipment and adequate ventilation should be utilized; personal hygiene should be observed; wash before eating or leaving a work site; be alert for signs of allergic reactions–seek prompt medical treatment if such reactions are suspected.

MIXING AND USE DIRECTIONS

Complete Swine Feeds Containing 0.0106% (96 g/t) Pyrantel Tartrate
Amount of Banminth 48 per Ton of Complete Feed | Resultant Use Level of PyranteTartrate in Complete Feed | Indications for Use
16.67 lb | 0.0881% (800g/t) | For the removal and control of large roundworm (A. suum) and nodular worm (Oesophagostomum)infections in swine.†

Directions for Use

As a single therapeutic treatment in complete feed; feed at the rate 1 lb of feed per 40 lb of body weight for animals up to 200 lb. For animals 200 lb or over, feed 5 lb of feed per head. Quantity of medicated feed required to treat pigs of various body weight is shown below:

Pig Weight (lb) | 20 | 40 | 60 | 80 | 100 | 200 and over
Quantity of Feed per Pig | 1/2 lb | 1 lb | 1 1/2 lb | 2 lb | 2 1/2 lb | 5 lb

Fast pigs overnight for optimum results. Pigs will generally consume this quantity of medicated feed within a few hours time after which regular feeding should be resumed. Better worming is achieved when pigs are separated by size into different lots or pens for treatment. Water should be made available to animals during fasting and treatment periods.

Complete Swine Feeds Containing 0.0106% (96 g/t) Pyrantel Tartrate
Amount of Banminth 48 per Ton of Complete Feed | Resultant Use Level of Pyrantel Tartrate in Complete Feed | Indications for Use | Directions for Use
2 lb | 0.0106% (96 g/t) | Aid in the prevention of migration and establishment of large roundworm (A. suum) infections; aid in the prevention of establishment of nodular worm (Oesophagostomum) infections in swine. | Feed continuously as the sole ration
2 lb | 0.0106% (96 g/t) | For the removal and control of large roundworm (Ascaris suum) infections in swine.† | Feed for 3 days as the sole ration.

Swine Protein Supplements for Further Dilution to Feed Containing 0.0106% (96 g/t) Pyrantel Tartrate
Amount of Banminth 48 per Ton of Protein Supplement* | Indications for Use | Directions
To calculate the amount of Banminth 48 per ton of protein supplement, divide 4000 by the quantity (lb) of protein supplement that will be mixed with grain(s) to produce a ton of complete feed, that is:; 4000 ÷ X = lb of Banminth 48 per ton of protein supplement.; where X = quantity (lb) of protein supplement that will be mixed with grain(s) to produce a ton of complete feed.; Example Calculation: Directions for use of the protein supplement require that 500 lb are to be mixed with grain(s) to produce a ton of complete feed.; 4000 ÷ 500 = 8 lb of Banminth 48 per; ton of protein supplement. | Aid in the prevention of migration and establishment of large roundworm (A. suum)infections; aid in the prevention of establishment of nodular worm (Oesophagostomum) infections in swine. | Prepare a complete feed by mixing proper quantities of protein supplement with grain(s). If pelleted, grind pellets before or during mixing. The resultant complete feed contains 0.0106% (96 g/t) pyrantel tartrate and is to be fed continuously as the sole ration.
To calculate the amount of Banminth 48 per ton of protein supplement, divide 4000 by the quantity (lb) of protein supplement that will be mixed with grain(s) to produce a ton of complete feed, that is:; 4000 ÷ X = lb of Banminth 48 per ton of protein supplement.; where X = quantity (lb) of protein supplement that will be mixed with grain(s) to produce a ton of complete feed.; Example Calculation: Directions for use of the protein supplement require that 500 lb are to be mixed with grain(s) to produce a ton of complete feed.; 4000 ÷ 500 = 8 lb of Banminth 48 per; ton of protein supplement. | For the removal and control of large roundworm (A. suum) infections in swine.† | Prepare a complete feed by mixing proper quantities of protein supplement with grain(s). If pelleted, grind pellets before or during mixing. The resultant complete feed contains 0.0106% (96 g/t) pyrantel tartrate and is to be fed for 3 days as the sole ration.

Swine Protein Supplements for Further Dilution to Feed Containing 0.0881% (800 g/t) Pyrantel Tartrate
Amount of Banminth 48 per Ton of Protein Supplement* | Indications for Use | Directions for Use
To calculate the amount of Banminth 48 per ton of protein supplement, divide 33,333 by the quantity (lb) of protein supplement that will be mixed with grain(s) to produce a ton of complete feed, that is:; 33,333 ÷ X = lb of Banminth 48 per ton of protein supplement.; where X = quantity (lb) of protein supplement that will be mixed with grain(s) to produce a ton of complete feed.; Example Calculation: Directions for use of the protein supplement require that 333 lb are to be mixed with grain(s) to produce a ton of complete feed.; 33,333 ÷ 333 = 100 lb of Banminth 48 per ton of protein supplement. | For the removal and control of large roundworm (A. suum)and nodular worm (Oesophagostomum) infections in swine.† | Prepare a complete feed by mixing the proper quantities of protein supplement with grain(s). If pelleted, grind pellets before or during mixing. The resultant complete feed contains 0.0881% (800 g/t) pyrantel tartrate and is to be fed as sole ration for a single therapeutic treatment at the rate of 1 lb of feed per 40 lb of body weight for animals up to 200 lb. For animals 200 lb or over, feed 5 lb of feed per head. Fast pigs overnight for optimum results. Pigs will generally consume this quantity of medicated feed within a few hours time, after which regular feeding should be resumed. Better worming is achieved when pigs are separated by size into different lots or pens for treatment. Water should be made available to animals during fasting and treatment periods.

* To find grams of pyrantel tartrate, multiply lb of Banminth by 48.

† Consult your veterinarian for assistance in the diagnosis, treatment, and control of parasitism.

WARNING:

Withdraw 24 hours prior to slaughter.

CAUTION: Consult your veterinarian before using in severely debilitated animals.

Do not mix in feeds containing bentonite.

NOT FOR HUMAN USE

RESTRICTED DRUG (CALIFORNIA) – USE ONLY AS DIRECTED

SEE BACK OF PACKAGE FOR FURTHER USE DIRECTIONS

Banminth® 48 is a Phibro Animal Health Corporation registered trademark for Pyrantel Tartrate

Phibro Animal Health Corporation, Teaneck, NJ 07666.

Net Weight: 50 lb (22.7 kg)

Approved by FDA under NADA #043-290

7909000

101-9015-07

U.S. Patent No. 3,549,624

Made in USA

Banminth 48